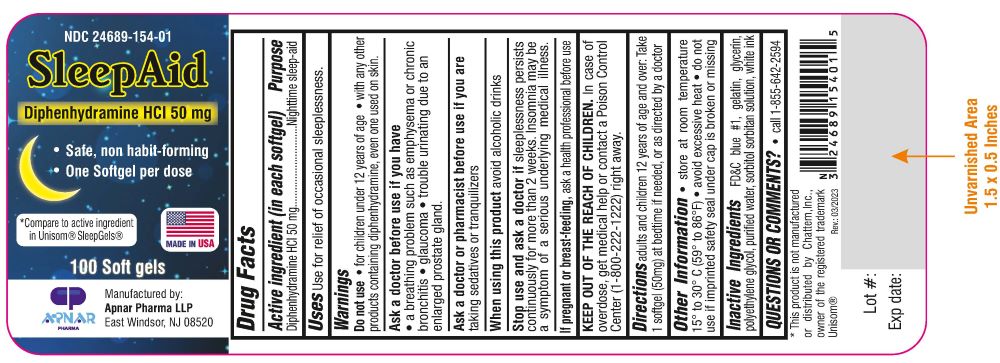 DRUG LABEL: SleepAid (Diphenhydramine HCL)
NDC: 24689-154 | Form: CAPSULE, LIQUID FILLED
Manufacturer: APNAR PHARMA LP
Category: otc | Type: HUMAN OTC DRUG LABEL
Date: 20250109

ACTIVE INGREDIENTS: DIPHENHYDRAMINE HYDROCHLORIDE 50 mg/1 1
INACTIVE INGREDIENTS: FD&C BLUE NO. 1; GLYCERIN; SORBITOL; GELATIN; POLYETHYLENE GLYCOL, UNSPECIFIED; SORBITAN; WATER

SleepAid (Diphenhydramine Hydrochloride 50mg Capsule,Liquid Filled)

DRUG FACTS

Active ingredient (in each soft gel)

Diphenhydramine HCL 50 mg

Purpose

Nighttime sleep-aid

USES

Use for relief of occasional sleeplessness.

Warnings

Do not use

- for children under 12 years of age
- with any other products containing diphenhydramine, even one used on skin.

Ask a doctor before use if you have

- a breathing problem such as emphysema or chronic bronchitis
- glaucoma
- trouble urinating due to an enlarged prostate gland.

Ask a doctor or pharmacist before use if you are

taking sedatives or tranquilizers.

When using this product

avoid alcoholic drinks

Stop use and ask a doctor if

sleeplessness persists continuously for more than 2 weeks. Insomnia may be a symptom of a serious underlying medical illness.

If pregnant or breast-feeding,

ask a health professional before use.

KEEP OUT OF THE REACH OF CHILDREN.

In case of overdose, get medical help or contact a Poison Control Center (1-800-222-1222) right away.

Directions

adults and children 12 years of age and over: Take 1 softgel (50 mg) at bedtime if needed, or as directed by a doctor

Other information

- store at room temperature 15º to 30º C (59º to 86º F)
- avoid excessive heat
- do not use if imprinted safety seal under cap is broken or missing

Inactive Ingredients

FD&C blue #1, gelatin, glycerin, polyethylene glycol, purified water, sorbitol sorbitan solution, white ink

Questions or comments?

- Call 1-855-642-2594

*Compare to active ingredient in Unisom® SleepGels®

*This product is not manufactured or distributed by Chattem, Inc., owner of the registered trademark Unisom®

Rev.: 03/2023

Manufactured by:

Apnar Pharma LLP

East Windsor, NJ 08520

PACKAGE LABEL

NDC 24689-154-01

SleepAid

Diphenhydramine HCL 50 mg

- Safe, non habit-forming
- One softgel per dose

Made in USA

100 Soft gels